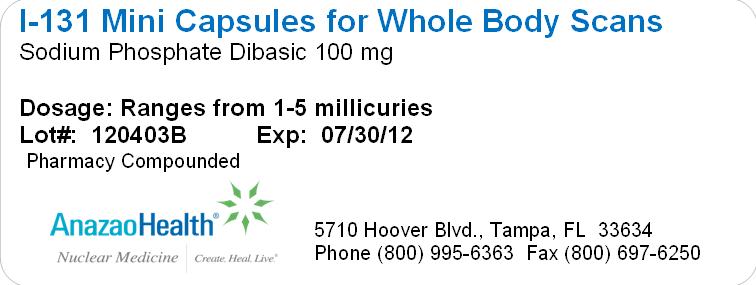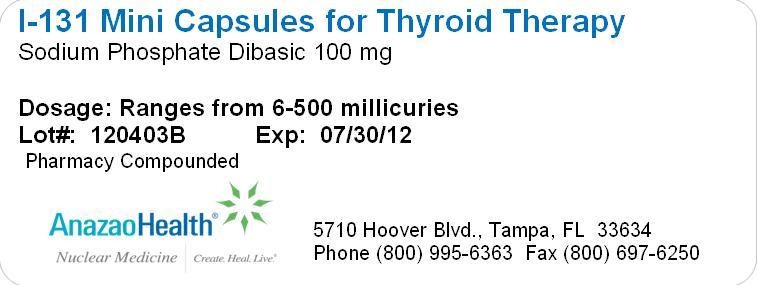 DRUG LABEL: I 131 Mini
NDC: 51808-119 | Form: CAPSULE
Manufacturer: AnazaoHealth Corporation
Category: prescription | Type: HUMAN PRESCRIPTION DRUG LABEL
Date: 20120523

ACTIVE INGREDIENTS: SODIUM IODIDE I-131 500 mCi/1 1
INACTIVE INGREDIENTS: SODIUM PHOSPHATE, DIBASIC 100 mg/1 1

I-131 Mini Caps
Medical Professional Information Sheet

Dear Medical Professional, Per your order, we have compounded I-131 in Mini Cap form. The characteristics of this compound are:

DESCRIPTION

Sodium Iodide I-131 (NaI-131) for therapeutic use is supplied for oral administration in small opaque white gelatin capsules, inside a blue and clear outer capsule. Each I-131 mini capsule is available in strengths ranging from (0.1 – 150 mCi) at the time of calibration. Iodine 131 decays by beta emission and associated gamma emission with a physical half-life of 8.04 days.

Sodium Iodide I-131 Mini Capsules are compounded by absorbing a solution of carrier-free sodium iodide I-131 into inert filler. The iodine 131 utilized in the preparation of the capsules contains not less than 99% Iodine-131 at the time of calibration.

Gelatin capsules are compounded per prescription requirements using high specific concentration I-131, allowing higher iodine activity in a small easy to swallow high activity capsule size. Capsules are formulated to rapidly dissolve in saline solution, to allow use for oral solution administration when clinically necessary.

CONTRAINDICATIONS AND ADVERSE REACTIONS

Radioiodine is excreted in human milk during lactation; breast feeding must be substituted during and following dose administration. Sodium Iodide 131 is not usually used for treatment of hyperthyroidism in patients under 30 years of age. Reactions to administration are rare; however potential side effects such as radiation sickness and bone marrow depression, acute leukemia, anemia, chromosomal abnormalities, acute thyroid crisis, blood dyscrasia, leukopenia, thrombocytopenia, and death represent potential side effects.

DOSAGE AND ADMINISTRATION

Anti-thyroid therapy of a severely hyperthyroid patient is usually discontinued three to four days before administration of radioiodide. For hyperthyroidism, the usual dose range is 4 to 10 mCi. Toxic nodular goiter and other special situations will require the use of larger doses. For thyroid carcinoma, 50 mCi is the usual dose for ablation of normal thyroid tissue, and 100 to 150 mCi is the usual subsequent therapeutic dose. Waterproof gloves should be used during the entire handling and administration procedure. Adequate shielding must be maintained.

CLINICAL UTILITY

Most patients with thyroid disease present with a thyroid nodule. Tools utilized to assess thyroid nodules and to rule out thyroid cancer include: serum thyroid function tests (TSH and thyroid hormone level), thyroid ultrasound (US), radionuclide scintigraphy (low activity I-131, I-123 and/or Tc99m), and fine needle aspiration (FNA) for cytology (cells) examination. High thyroid hormone levels (T4 or T3) and a low TSH level may indicate a nodule is a benign hyperfunctioning nodule (adenoma), thereby tending to rule out thyroid cancer. In such cases, thyroid imaging (US or scintigraphy) determines whether the nodule is hyperfunctioning whereas thyroid cancers appear under-functioning or “cold” on the scan. Graves’ disease and Hashimotos’ thyroiditis represent thyroid diseases which occur in children who have autoimmune thyroid disease. In these patients, abnormal thyroid function tests reflect underlying thyroid disease but do not exclude thyroid cancer.

The administration of radioiodine has proved to be an excellent method of destruction of over functioning thyroid tissue (either diffuse or toxic nodular goiter). Radioiodine is concentrated in the thyroid, destroying cells that concentrate it.

Surgical removal is the treatment of choice for thyroid carcinomas. At 2 to 4 months post surgery, a whole-body I-131 scan is performed following cessation of thyroxin drug for 4-6 weeks prior to the scan, thereby causing hypothyroidism; TSH then rises and stimulates iodide uptake. Iodine-containing foods and contrast media are avoided. Patients with significant I-131 uptake are given ablative (100 - 150 mCi) doses of I-131. For minimal uptake, doses of 30-50 mCi I-131 are given on an outpatient basis. Patients with extra thyroidal uptake from metastatic disease may be given larger doses of greater than 100 mCi.

I-131 THERAPY CAPSULE MARKET BACKGROUND

I-131 Therapy Capsule formulations provide an enhanced safety profile for nuclear medicine professionals. Oral solutions raise the risk for spills during administration in addition to the not uncommon scenario where very ill patients reject oral solution treatment; whereupon vomiting episodes create large areas of high level radiation spill. Oral solutions, however, are sold at deep discounts as compared to Therapy Capsules.

While many U.S. facilities have moved to adopt ALARA recommendations to reduce radiation exposure to healthcare workers which reasonably include routinely ordering encapsulated high activity I-131; the scenario also exists that the intended patient may not be able to swallow the Therapy Capsule for reasons including: the large size of competitive suppliers, as well as intubated, quadriplegia and/or severe swallowing difficulties. In these instances, it is particularly beneficial to have the ability to dissolve the capsule so that the patient may be treated on the same day, without having to order additional preparation.

Thank you,

AnazaoHealth Corporation